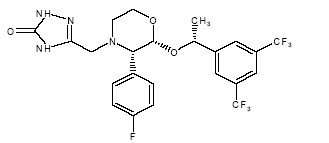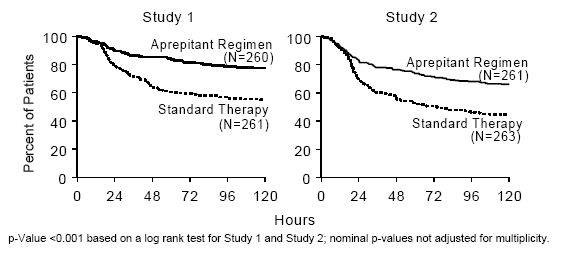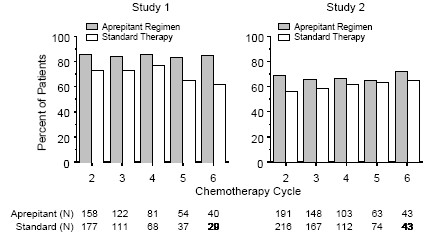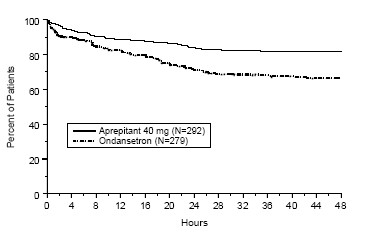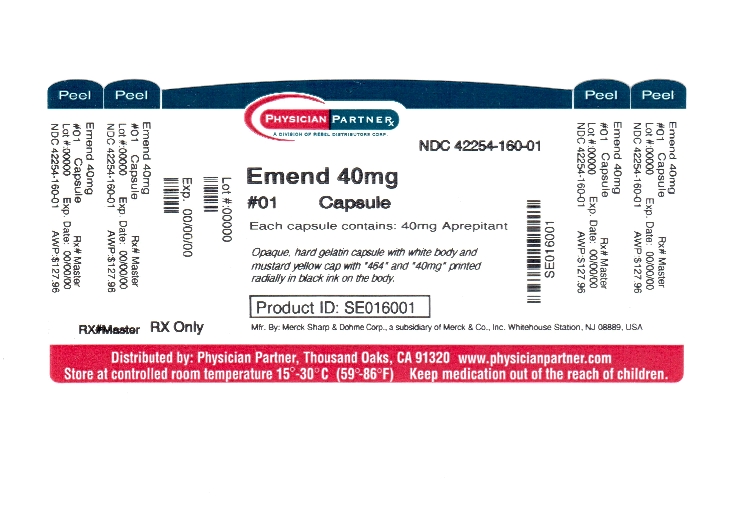 DRUG LABEL: EMEND
NDC: 42254-160 | Form: CAPSULE
Manufacturer: Rebel Distributors Corp
Category: prescription | Type: HUMAN PRESCRIPTION DRUG LABEL
Date: 20120223

ACTIVE INGREDIENTS: aprepitant 40 mg/1 1
INACTIVE INGREDIENTS: sucrose; CELLULOSE, MICROCRYSTALLINE; hydroxypropyl cellulose; sodium lauryl sulfate; gelatin; titanium dioxide; silicon dioxide; FERRIC OXIDE YELLOW

HIGHLIGHTS OF PRESCRIBING INFORMATION

These highlights do not include all the information needed to use EMEND safely and effectively. See full prescribing information for EMEND.
EMEND (aprepitant) Capsules
Initial U.S. Approval: 2003

1 INDICATIONS AND USAGE

EMEND® is a substance P/neurokinin 1 (NK1) receptor antagonist, indicated:

- in combination with other antiemetic agents for the:
  - prevention of acute and delayed nausea and vomiting associated with initial and repeat courses of highly emetogenic cancer chemotherapy (HEC) including high-dose cisplatin (1.1)
  - prevention of nausea and vomiting associated with initial and repeat courses of moderately emetogenic cancer chemotherapy (MEC) (1.1)
- for the prevention of postoperative nausea and vomiting (PONV) (1.2)

Limitations of Use (1.3)

- Not studied for the treatment of established nausea and vomiting.
- Chronic continuous administration is not recommended.

2 DOSAGE AND ADMINISTRATION

Prevention of Chemotherapy Induced Nausea and Vomiting (2.1)

- EMEND is given for 3 days as part of the chemotherapy induced nausea and vomiting (CINV) regimen that includes a corticosteroid and a 5-HT3 antagonist. (2.1)
  - The recommended dose of EMEND is 125 mg orally 1 hour prior to chemotherapy treatment (Day 1) and 80 mg orally once daily in the morning on Days 2 and 3. (2.1)
  - EMEND (fosaprepitant dimeglumine) for Injection may be substituted for oral EMEND (125 mg) on Day 1 only as part of the CINV regimen. (2.1)

Prevention of Postoperative Nausea and Vomiting (2.2)

- The recommended oral dosage of EMEND for the postoperative nausea and vomiting (PONV) indication is 40 mg within 3 hours prior to induction of anesthesia. (2.2)

3 DOSAGE FORMS AND STRENGTHS

Capsules: 40 mg; 80 mg; 125 mg (3)

4 CONTRAINDICATIONS

- Hypersensitivity to any component of this medication. (4, 6.2)
- EMEND should not be used concurrently with pimozide, terfenadine, astemizole, or cisapride, since inhibition of CYP3A4 by aprepitant could result in elevated plasma concentrations of these drugs, potentially causing serious or life-threatening reactions. (4)

5 WARNINGS AND PRECAUTIONS

- Coadministration of aprepitant with warfarin (a CYP2C9 substrate) may result in a clinically significant decrease in International Normalized Ratio (INR) of prothrombin time. (5.2)
- The efficacy of hormonal contraceptives during and for 28 days following the last dose of EMEND may be reduced. Alternative or back-up methods of contraception should be used. (5.3, 7.1)
- EMEND is a dose-dependent inhibitor of CYP3A4, and should be used with caution in patients receiving concomitant medications that are primarily metabolized through CYP3A4. (5.1)
- Caution should be exercised when administered in patients with severe hepatic impairment. (2.5, 5.4, 12.3)

6 ADVERSE REACTIONS

- Clinical adverse experiences for the CINV regimen in conjunction with highly and moderately emetogenic chemotherapy (incidence >10%) are: alopecia, anorexia, asthenia/fatigue, constipation, diarrhea, headache, hiccups, nausea. (6.1)
- Clinical adverse experiences for the PONV regimen (incidence >5%) are: constipation, hypotension, nausea, pruritus, pyrexia. (6.1)

To report SUSPECTED ADVERSE REACTIONS, contact Merck Sharp & Dohme Corp., a subsidiary of Merck & Co., Inc., at 1-877-888-4231 or FDA at 1-800-FDA-1088 or www.fda.gov/medwatch.

7 DRUG INTERACTIONS

- Aprepitant is a substrate for CYP3A4; therefore, coadministration of EMEND with drugs that inhibit or induce CYP3A4 activity may result in increased or reduced plasma concentrations of aprepitant, respectively. (5.1, 7.1, 7.2).
- Aprepitant is an inducer of CYP2C9; therefore, coadministration of EMEND with drugs that are metabolized by CYP2C9 (e.g. warfarin, tolbutamide), may result in lower plasma concentrations of these drugs. (5.2, 7.1)

FULL PRESCRIBING INFORMATION

1 INDICATIONS AND USAGE

1.1 Prevention of Chemotherapy Induced Nausea and Vomiting (CINV)

EMEND [Registered trademark of Merck Sharp & Dohme Corp., a subsidiary of Merck & Co., Inc. Copyright © 2003, 2005, 2006 Merck Sharp & Dohme Corp., a subsidiary of Merck & Co., Inc. All Rights Reserved] , in combination with other antiemetic agents, is indicated for the:

- prevention of acute and delayed nausea and vomiting associated with initial and repeat courses of highly emetogenic cancer chemotherapy (HEC) including high-dose cisplatin
- prevention of nausea and vomiting associated with initial and repeat courses of moderately emetogenic cancer chemotherapy (MEC) [see Dosage and Administration (2.1)].

1.2 Prevention of Postoperative Nausea and Vomiting (PONV)

EMEND is indicated for the prevention of postoperative nausea and vomiting [see Dosage and Administration (2.2)].

1.3 Limitations of Use

EMEND has not been studied for the treatment of established nausea and vomiting.

Chronic continuous administration is not recommended [see Warnings and Precautions (5.5)].

2 DOSAGE AND ADMINISTRATION

2.1 Prevention of Chemotherapy Induced Nausea and Vomiting (CINV)

Capsules of EMEND (aprepitant) are given for 3 days as part of a regimen that includes a corticosteroid and a 5-HT3 antagonist. The recommended dose of EMEND is 125 mg orally 1 hour prior to chemotherapy treatment (Day 1) and 80 mg orally once daily in the morning on Days 2 and 3.

EMEND may be taken with or without food.

EMEND (fosaprepitant dimeglumine) for Injection (115 mg) is a prodrug of aprepitant and may be substituted for oral EMEND (125 mg), 30 minutes prior to chemotherapy, on Day 1 only of the CINV regimen as an intravenous infusion administered over 15 minutes.

In clinical studies with EMEND, the following regimen was used for the prevention of nausea and vomiting associated with highly emetogenic cancer chemotherapy:

 | Day 1 | Day 2 | Day 3 | Day 4
EMEND [EMEND was administered orally 1 hour prior to chemotherapy treatment on Day 1 and in the morning on Days 2 and 3.] | 125 mg orally | 80 mg orally | 80 mg orally | none
Dexamethasone [Dexamethasone was administered 30 minutes prior to chemotherapy treatment on Day 1 and in the morning on Days 2 through 4. The dose of dexamethasone was chosen to account for drug interactions.] | 12 mg orally | 8 mg orally | 8 mg orally | 8 mg orally
Ondansetron [Ondansetron was administered 30 minutes prior to chemotherapy treatment on Day 1.] | 32 mg I.V. | none | none | none

In a clinical study with EMEND, the following regimen was used for the prevention of nausea and vomiting associated with moderately emetogenic cancer chemotherapy:

 | Day 1 | Day 2 | Day 3
EMEND [EMEND was administered orally 1 hour prior to chemotherapy treatment on Day 1 and in the morning on Days 2 and 3.] | 125 mg orally | 80 mg orally | 80 mg orally
Dexamethasone [Dexamethasone was administered 30 minutes prior to chemotherapy treatment on Day 1. The dose of dexamethasone was chosen to account for drug interactions.] | 12 mg orally | none | none
Ondansetron [Ondansetron 8-mg capsule was administered 30 to 60 minutes prior to chemotherapy treatment and one 8-mg capsule was administered 8 hours after the first dose on Day 1.] | 2 x 8 mg orally | none | none

2.2 Prevention of Postoperative Nausea and Vomiting (PONV)

The recommended oral dosage of EMEND is 40 mg within 3 hours prior to induction of anesthesia.

EMEND may be taken with or without food.

2.3 Geriatric Patients

No dosage adjustment is necessary for the elderly.

2.4 Patients with Renal Impairment

No dosage adjustment is necessary for patients with renal impairment or for patients with end stage renal disease (ESRD) undergoing hemodialysis.

2.5 Patients with Hepatic Impairment

No dosage adjustment is necessary for patients with mild to moderate hepatic impairment (Child-Pugh score 5 to 9). There are no clinical data in patients with severe hepatic impairment (Child-Pugh score >9).

2.6 Coadministration with Other Drugs

For additional information on dose adjustment for corticosteroids when coadministered with EMEND, see Drug Interactions (7.1).

Refer to the full prescribing information for coadministered antiemetic agents.

3 DOSAGE FORMS AND STRENGTHS

- Capsules EMEND 40 mg are opaque, hard, gelatin capsules, with white body and mustard yellow cap with “464” and “40 mg” printed radially in black ink on the body.
- Capsules EMEND 80 mg are white, opaque, hard, gelatin capsules, with “461” and “80 mg” printed radially in black ink on the body.
- Capsules EMEND 125 mg are opaque, hard, gelatin capsules, with white body and pink cap with “462” and “125 mg” printed radially in black ink on the body.

4 CONTRAINDICATIONS

EMEND is contraindicated in patients who are hypersensitive to any component of the product.

EMEND is a dose-dependent inhibitor of cytochrome P450 isoenzyme 3A4 (CYP3A4). EMEND should not be used concurrently with pimozide, terfenadine, astemizole, or cisapride. Inhibition of CYP3A4 by aprepitant could result in elevated plasma concentrations of these drugs, potentially causing serious or life-threatening reactions [see Drug Interactions (7.1)].

5 WARNINGS AND PRECAUTIONS

5.1 CYP3A4 Interactions

EMEND (aprepitant), a dose-dependent inhibitor of CYP3A4, should be used with caution in patients receiving concomitant medications that are primarily metabolized through CYP3A4. Moderate inhibition of CYP3A4 by aprepitant, 125 mg/80 mg regimen, could result in elevated plasma concentrations of these concomitant medications.

Weak inhibition of CYP3A4 by a single 40 mg dose of aprepitant is not expected to alter the plasma concentrations of concomitant medications that are primarily metabolized through CYP3A4 to a clinically significant degree.

When aprepitant is used concomitantly with another CYP3A4 inhibitor, aprepitant plasma concentrations could be elevated. When EMEND is used concomitantly with medications that induce CYP3A4 activity, aprepitant plasma concentrations could be reduced and this may result in decreased efficacy of EMEND [see Drug Interactions (7.1)].

Chemotherapy agents that are known to be metabolized by CYP3A4 include docetaxel, paclitaxel, etoposide, irinotecan, ifosfamide, imatinib, vinorelbine, vinblastine and vincristine. In clinical studies, EMEND (125 mg/80 mg regimen) was administered commonly with etoposide, vinorelbine, or paclitaxel. The doses of these agents were not adjusted to account for potential drug interactions.

In separate pharmacokinetic studies no clinically significant change in docetaxel or vinorelbine pharmacokinetics was observed when EMEND (125 mg/80 mg regimen) was co-administered.

Due to the small number of patients in clinical studies who received the CYP3A4 substrates vinblastine, vincristine, or ifosfamide, particular caution and careful monitoring are advised in patients receiving these agents or other chemotherapy agents metabolized primarily by CYP3A4 that were not studied [see Drug Interactions (7.1)].

5.2 Coadministration with Warfarin (a CYP2C9 substrate)

Coadministration of EMEND with warfarin may result in a clinically significant decrease in International Normalized Ratio (INR) of prothrombin time. In patients on chronic warfarin therapy, the INR should be closely monitored in the 2-week period, particularly at 7 to 10 days, following initiation of the 3-day regimen of EMEND with each chemotherapy cycle, or following administration of a single 40 mg dose of EMEND for the prevention of postoperative nausea and vomiting [see Drug Interactions (7.1)].

5.3 Coadministration with Hormonal Contraceptives

Upon coadministration with EMEND, the efficacy of hormonal contraceptives during and for 28 days following the last dose of EMEND may be reduced. Alternative or back-up methods of contraception should be used during treatment with EMEND and for 1 month following the last dose of EMEND [see Drug Interactions (7.1)].

5.4 Patients with Severe Hepatic Impairment

There are no clinical or pharmacokinetic data in patients with severe hepatic impairment (Child-Pugh score >9). Therefore, caution should be exercised when EMEND is administered in these patients [see Clinical Pharmacology (12.3) and Dosage and Administration (2.5)].

5.5 Chronic Continuous Use

Chronic continuous use of EMEND for prevention of nausea and vomiting is not recommended because it has not been studied; and because the drug interaction profile may change during chronic continuous use.

6 ADVERSE REACTIONS

The overall safety of aprepitant was evaluated in approximately 5300 individuals.

Because clinical trials are conducted under widely varying conditions, adverse reaction rates observed in the clinical trials of a drug cannot be directly compared to rates in the clinical trials of another drug and may not reflect the rates observed in clinical practice.

6.1 Clinical Trials Experience

Chemotherapy Induced Nausea and Vomiting

Highly Emetogenic Chemotherapy

In 2 well-controlled clinical trials in patients receiving highly emetogenic cancer chemotherapy, 544 patients were treated with aprepitant during Cycle 1 of chemotherapy and 413 of these patients continued into the Multiple-Cycle extension for up to 6 cycles of chemotherapy. EMEND was given in combination with ondansetron and dexamethasone.

In Cycle 1, clinical adverse experiences were reported in approximately 69% of patients treated with the aprepitant regimen compared with approximately 68% of patients treated with standard therapy. Table 1 shows the percent of patients with clinical adverse experiences reported at an incidence ≥3%.

Table 1: Percent of Patients Receiving Highly Emetogenic Chemotherapy with Clinical Adverse Experiences (Incidence ≥3%) — Cycle 1
 | Aprepitant Regimen (N = 544) | Standard Therapy (N = 550)
Body as a Whole/Site Unspecified
Asthenia/Fatigue; Dizziness; Dehydration; Abdominal Pain; Fever; Mucous Membrane Disorder | 17.8; 6.6; 5.9; 4.6; 2.9; 2.6 | 11.8; 4.4; 5.1; 3.3; 3.5; 3.1
Digestive System
Nausea; Constipation; Diarrhea; Vomiting; Heartburn; Gastritis; Epigastric Discomfort | 12.7; 10.3; 10.3; 7.5; 5.3; 4.2; 4.0 | 11.8; 12.2; 7.5; 7.6; 4.9; 3.1; 3.1
Eyes, Ears, Nose, and Throat
Tinnitus | 3.7 | 3.8
Hemic and Lymphatic System
Neutropenia | 3.1 | 2.9
Metabolism and Nutrition
Anorexia | 10.1 | 9.5
Nervous System
Headache; Insomnia | 8.5; 2.9 | 8.7; 3.1
Respiratory System
Hiccups | 10.8 | 5.6

In addition, isolated cases of serious adverse experiences, regardless of causality, of bradycardia, disorientation, and perforating duodenal ulcer were reported in highly emetogenic CINV clinical studies.

Moderately Emetogenic Chemotherapy

During Cycle 1 of 2 moderately emetogenic chemotherapy studies, 868 patients were treated with the aprepitant regimen and 686 of these patients continued into extensions for up to 4 cycles of chemotherapy. In the combined analysis of Cycle 1 data for these 2 studies, adverse experiences were reported in approximately 69% of patients treated with the aprepitant regimen compared with approximately 72% of patients treated with standard therapy.

In the combined analysis of Cycle 1 data for these 2 studies, the adverse experience profile in both moderately emetogenic chemotherapy studies was generally comparable to the highly emetogenic chemotherapy studies. Table 2 shows the percent of patients with clinical adverse experiences reported at an incidence ≥3%.

Table 2: Percent of Patients Receiving Moderately Emetogenic Chemotherapy with Clinical Adverse Experiences (Incidence ≥3%) — Cycle 1
 | Aprepitant Regimen (N = 868) | Standard Therapy (N = 846)
Blood and Lymphatic System Disorders
Neutropenia | 5.8 | 5.6
Metabolism and Nutrition Disorders
Anorexia | 6.2 | 7.2
Psychiatric Disorders
Insomnia | 2.6 | 3.7
Nervous System Disorders
Headache; Dizziness | 13.2; 2.8 | 14.3; 3.4
Gastrointestinal Disorders
Constipation; Diarrhea; Dyspepsia; Nausea; Stomatitis | 10.3; 7.6; 5.8; 5.8; 3.1 | 15.5; 8.7; 3.8; 5.1; 2.7
Skin and Subcutaneous Tissue Disorders
Alopecia | 12.4 | 11.9
General Disorders and General Administration Site Conditions
Fatigue; Asthenia | 15.4; 4.7 | 15.6; 4.6

In a combined analysis of these two studies, isolated cases of serious adverse experiences were similar in the two treatment groups.

Highly and Moderately Emetogenic Chemotherapy

The following additional clinical adverse experiences (incidence >0.5% and greater than standard therapy), regardless of causality, were reported in patients treated with aprepitant regimen in either HEC or MEC studies:

Infections and infestations: candidiasis, herpes simplex, lower respiratory infection, oral candidiasis, pharyngitis, septic shock, upper respiratory infection, urinary tract infection.

Neoplasms benign, malignant and unspecified (including cysts and polyps): malignant neoplasm, non-small cell lung carcinoma.

Blood and lymphatic system disorders: anemia, febrile neutropenia, thrombocytopenia.

Metabolism and nutrition disorders: appetite decreased, diabetes mellitus, hypokalemia.

Psychiatric disorders: anxiety disorder, confusion, depression.

Nervous system: peripheral neuropathy, sensory neuropathy, taste disturbance, tremor.

Eye disorders: conjunctivitis.

Cardiac disorders: myocardial infarction, palpitations, tachycardia.

Vascular disorders: deep venous thrombosis, flushing, hot flush, hypertension, hypotension.

Respiratory, thoracic and mediastinal disorders: cough, dyspnea, nasal secretion, pharyngolaryngeal pain, pneumonitis, pulmonary embolism, respiratory insufficiency, vocal disturbance.

Gastrointestinal disorders: abdominal pain upper, acid reflux, deglutition disorder, dry mouth, dysgeusia, dysphagia, eructation, flatulence, obstipation, salivation increased.

Skin and subcutaneous tissue disorders: acne, diaphoresis, pruritus, rash.

Musculoskeletal and connective tissue disorders: arthralgia, back pain, muscular weakness, musculoskeletal pain, myalgia.

Renal and urinary disorders: dysuria, renal insufficiency.

Reproductive system and breast disorders: pelvic pain.

General disorders and administrative site conditions: edema, malaise, pain, rigors.

Investigations: weight loss.

Stevens-Johnson syndrome was reported as a serious adverse experience in a patient receiving aprepitant with cancer chemotherapy in another CINV study.

Laboratory Adverse Experiences

Table 3 shows the percent of patients with laboratory adverse experiences reported at an incidence ≥3% in patients receiving highly emetogenic chemotherapy.

Table 3: Percent of Patients Receiving Highly Emetogenic Chemotherapy with Laboratory Adverse Experiences (Incidence ≥3%) — Cycle 1
 | Aprepitant Regimen (N = 544) | Standard Therapy (N = 550)
Proteinuria; ALT Increased; Blood Urea Nitrogen Increased; Serum Creatinine Increased; AST Increased | 6.8; 6.0; 4.7; 3.7; 3.0 | 5.3; 4.3; 3.5; 4.3; 1.3

The following additional laboratory adverse experiences (incidence >0.5% and greater than standard therapy), regardless of causality, were reported in patients treated with aprepitant regimen: alkaline phosphatase increased, hyperglycemia, hyponatremia, leukocytes increased, erythrocyturia, leukocyturia.

The adverse experience profiles in the Multiple-Cycle extensions of HEC and MEC studies for up to 6 cycles of chemotherapy were generally similar to that observed in Cycle 1.

Postoperative Nausea and Vomiting

In well-controlled clinical studies in patients receiving general anesthesia, 564 patients were administered 40 mg aprepitant orally and 538 patients were administered 4 mg ondansetron IV.

Clinical adverse experiences were reported in approximately 60% of patients treated with 40 mg aprepitant compared with approximately 64% of patients treated with 4 mg ondansetron IV. Table 4 shows the percent of patients with clinical adverse experiences reported at an incidence ≥3% of the combined studies.

Table 4: Percent of Patients Receiving General Anesthesia with Clinical Adverse Experiences (Incidence ≥3%)
 | Aprepitant 40 mg (N = 564) | Ondansetron (N = 538)
Infections and Infestations
Urinary Tract Infection | 2.3 | 3.2
Blood and Lymphatic System Disorders
Anemia | 3.0 | 4.3
Psychiatric Disorders
Insomnia | 2.1 | 3.3
Nervous System Disorders
Headache | 5.0 | 6.5
Cardiac Disorders
Bradycardia | 4.4 | 3.9
Vascular Disorders
Hypotension; Hypertension | 5.7; 2.1 | 4.6; 3.2
Gastrointestinal Disorders
Nausea; Constipation; Flatulence; Vomiting | 8.5; 8.5; 4.1; 2.5 | 8.6; 7.6; 5.8; 3.9
Skin and Subcutaneous Tissue Disorders
Pruritus | 7.6 | 8.4
General Disorders and General Administration Site Conditions
Pyrexia | 5.9 | 10.6

The following additional clinical adverse experiences (incidence >0.5% and greater than ondansetron), regardless of causality, were reported in patients treated with aprepitant:

Infections and infestations: postoperative infection

Metabolism and nutrition disorders: hypokalemia, hypovolemia.

Nervous system disorders: dizziness, hypoesthesia, syncope.

Vascular disorders: hematoma

Respiratory, thoracic and mediastinal disorders: dyspnea, hypoxia, respiratory depression.

Gastrointestinal disorders: abdominal pain, abdominal pain upper, dry mouth, dyspepsia.

Skin and subcutaneous tissue disorders: urticaria

General disorders and administrative site conditions: hypothermia, pain.

Investigations: blood pressure decreased

Injury, poisoning and procedural complications: operative hemorrhage, wound dehiscence.

Other adverse experiences (incidence ≤0.5%) reported in patients treated with aprepitant 40 mg for postoperative nausea and vomiting included:

Nervous system disorders: dysarthria, sensory disturbance.

Eye disorders: miosis, visual acuity reduced.

Respiratory, thoracic and mediastinal disorders: wheezing

Gastrointestinal disorders: bowel sounds abnormal, stomach discomfort.

There were no serious adverse drug-related experiences reported in the postoperative nausea and vomiting clinical studies in patients taking 40 mg aprepitant.

Laboratory Adverse Experiences

One laboratory adverse experience, hemoglobin decreased (40 mg aprepitant 3.8%, ondansetron 4.2%), was reported at an incidence ≥3% in a patient receiving general anesthesia.

The following additional laboratory adverse experiences (incidence >0.5% and greater than ondansetron), regardless of causality, were reported in patients treated with aprepitant 40 mg: blood albumin decreased, blood bilirubin increased, blood glucose increased, blood potassium decreased, glucose urine present.

The adverse experience of ALT increased occurred with similar incidence in patients treated with aprepitant 40 mg (1.1%) as in patients treated with ondansetron 4 mg (1.0%).

Other Studies

In addition, two serious adverse experiences were reported in postoperative nausea and vomiting (PONV) clinical studies in patients taking a higher dose of aprepitant: one case of constipation, and one case of sub-ileus.

Angioedema and urticaria were reported as serious adverse experiences in a patient receiving aprepitant in a non-CINV/non-PONV study.

6.2 Postmarketing Experience

The following adverse reactions have been identified during postmarketing use of aprepitant. Because these reactions are reported voluntarily from a population of uncertain size, it is generally not possible to reliably estimate their frequency or establish a causal relationship to the drug.

Skin and subcutaneous tissue disorders: pruritus, rash, urticaria, rarely Stevens-Johnson syndrome/toxic epidermal necrolysis.

Immune system disorders: hypersensitivity reactions including anaphylactic reactions.

7 DRUG INTERACTIONS

Aprepitant is a substrate, a weak-to-moderate (dose-dependent) inhibitor, and an inducer of CYP3A4. Aprepitant is also an inducer of CYP2C9.

7.1 Effect of Aprepitant on the Pharmacokinetics of Other Agents

CYP3A4 Substrates:

Weak inhibition of CYP3A4 by a single 40 mg dose of aprepitant is not expected to alter the plasma concentrations of concomitant medications that are primarily metabolized through CYP3A4 to a clinically significant degree. However, higher aprepitant doses or repeated dosing at any aprepitant dose may have a clinically significant effect.

As a moderate inhibitor of CYP3A4 at a dose of 125 mg/80 mg, aprepitant can increase plasma concentrations of concomitantly administered oral medications that are metabolized through CYP3A4 [see Contraindications (4)]. The use of fosaprepitant may increase CYP3A4 substrate plasma concentrations to a lesser degree than the use of oral aprepitant (125 mg).

5-HT3 antagonists: In clinical drug interaction studies, aprepitant did not have clinically important effects on the pharmacokinetics of ondansetron, granisetron, or hydrodolasetron (the active metabolite of dolasetron).

Corticosteroids:

Dexamethasone: EMEND, when given as a regimen of 125 mg with dexamethasone coadministered orally as 20 mg on Day 1, and EMEND when given as 80 mg/day with dexamethasone coadministered orally as 8 mg on Days 2 through 5, increased the AUC of dexamethasone, a CYP3A4 substrate, by 2.2-fold on Days 1 and 5. The oral dexamethasone doses should be reduced by approximately 50% when coadministered with EMEND (125 mg/80 mg regimen), to achieve exposures of dexamethasone similar to those obtained when it is given without EMEND. The daily dose of dexamethasone administered in clinical chemotherapy induced nausea and vomiting studies with EMEND reflects an approximate 50% reduction of the dose of dexamethasone [see Dosage and Administration (2.1)]. A single dose of EMEND (40 mg) when coadministered with a single oral dose of dexamethasone 20 mg, increased the AUC of dexamethasone by 1.45-fold. Therefore, no dose adjustment is recommended.

Methylprednisolone: EMEND, when given as a regimen of 125 mg on Day 1 and 80 mg/day on Days 2 and 3, increased the AUC of methylprednisolone, a CYP3A4 substrate, by 1.34-fold on Day 1 and by 2.5-fold on Day 3, when methylprednisolone was coadministered intravenously as 125 mg on Day 1 and orally as 40 mg on Days 2 and 3. The IV methylprednisolone dose should be reduced by approximately 25%, and the oral methylprednisolone dose should be reduced by approximately 50% when coadministered with EMEND (125 mg/80 mg regimen) to achieve exposures of methylprednisolone similar to those obtained when it is given without EMEND. Although the concomitant administration of methylprednisolone with the single 40 mg dose of aprepitant has not been studied, a single 40 mg dose of EMEND produces a weak inhibition of CYP3A4 (based on midazolam interaction study) and it is not expected to alter the plasma concentrations of methylprednisolone to a clinically significant degree. Therefore, no dose adjustment is recommended.

Chemotherapeutic agents: [see Warnings and Precautions (5.1)]

Docetaxel: In a pharmacokinetic study, EMEND (125 mg/80 mg regimen) did not influence the pharmacokinetics of docetaxel.

Vinorelbine: In a pharmacokinetic study, EMEND (125 mg/80 mg regimen) did not influence the pharmacokinetics of vinorelbine to a clinically significant degree.

CYP2C9 Substrates (Warfarin, Tolbutamide):

Aprepitant has been shown to induce the metabolism of S(-) warfarin and tolbutamide, which are metabolized through CYP2C9. Coadministration of EMEND with these drugs or other drugs that are known to be metabolized by CYP2C9, such as phenytoin, may result in lower plasma concentrations of these drugs.

Warfarin: A single 125-mg dose of EMEND was administered on Day 1 and 80 mg/day on Days 2 and 3 to healthy subjects who were stabilized on chronic warfarin therapy. Although there was no effect of EMEND on the plasma AUC of R(+) or S(-) warfarin determined on Day 3, there was a 34% decrease in S(-) warfarin (a CYP2C9 substrate) trough concentration accompanied by a 14% decrease in the prothrombin time (reported as International Normalized Ratio or INR) 5 days after completion of dosing with EMEND. In patients on chronic warfarin therapy, the prothrombin time (INR) should be closely monitored in the 2-week period, particularly at 7 to 10 days, following initiation of the 3-day regimen of EMEND with each chemotherapy cycle, or following administration of a single 40 mg dose of EMEND for the prevention of postoperative nausea and vomiting.

Tolbutamide: EMEND, when given as 125 mg on Day 1 and 80 mg/day on Days 2 and 3, decreased the AUC of tolbutamide (a CYP2C9 substrate) by 23% on Day 4, 28% on Day 8, and 15% on Day 15, when a single dose of tolbutamide 500 mg was administered orally prior to the administration of the 3-day regimen of EMEND and on Days 4, 8, and 15.

EMEND, when given as a 40-mg single oral dose on Day 1, decreased the AUC of tolbutamide (a CYP2C9 substrate) by 8% on Day 2, 16% on Day 4, 15% on Day 8, and 10% on Day 15, when a single dose of tolbutamide 500 mg was administered orally prior to the administration of EMEND 40 mg and on Days 2, 4, 8, and 15. This effect was not considered clinically important.

Oral contraceptives: Aprepitant, when given once daily for 14 days as a 100-mg capsule with an oral contraceptive containing 35 mcg of ethinyl estradiol and 1 mg of norethindrone, decreased the AUC of ethinyl estradiol by 43%, and decreased the AUC of norethindrone by 8%.

In another study, a daily dose of an oral contraceptive containing ethinyl estradiol and norethindrone was administered on Days 1 through 21, and EMEND was given as a 3-day regimen of 125 mg on Day 8 and 80 mg/day on Days 9 and 10 with ondansetron 32 mg IV on Day 8 and oral dexamethasone given as 12 mg on Day 8 and 8 mg/day on Days 9, 10, and 11. In the study, the AUC of ethinyl estradiol decreased by 19% on Day 10 and there was as much as a 64% decrease in ethinyl estradiol trough concentrations during Days 9 through 21. While there was no effect of EMEND on the AUC of norethindrone on Day 10, there was as much as a 60% decrease in norethindrone trough concentrations during Days 9 through 21.

In another study, a daily dose of an oral contraceptive containing ethinyl estradiol and norgestimate (which is converted to norelgestromin) was administered on Days 1 through 21, and EMEND 40 mg was given on Day 8. In the study, the AUC of ethinyl estradiol decreased by 4% and 29% on Day 8 and Day 12, respectively, while the AUC of norelgestromin increased by 18% on Day 8 and decreased by 10% on Day 12. In addition, the trough concentrations of ethinyl estradiol and norelgestromin on Days 8 through 21 were generally lower following coadministration of the oral contraceptive with EMEND 40 mg on Day 8 compared to the trough levels following administration of the oral contraceptive alone.

The coadministration of EMEND may reduce the efficacy of hormonal contraceptives (these can include birth control pills, skin patches, implants, and certain IUDs) during and for 28 days after administration of the last dose of EMEND. Alternative or back-up methods of contraception should be used during treatment with EMEND and for 1 month following the last dose of EMEND.

Midazolam: EMEND increased the AUC of midazolam, a sensitive CYP3A4 substrate, by 2.3-fold on Day 1 and 3.3-fold on Day 5, when a single oral dose of midazolam 2 mg was coadministered on Day 1 and Day 5 of a regimen of EMEND 125 mg on Day 1 and 80 mg/day on Days 2 through 5. The potential effects of increased plasma concentrations of midazolam or other benzodiazepines metabolized via CYP3A4 (alprazolam, triazolam) should be considered when coadministering these agents with EMEND (125 mg/80 mg). A single dose of EMEND (40 mg) increased the AUC of midazolam by 1.2-fold on Day 1, when a single oral dose of midazolam 2 mg was coadministered on Day 1 with EMEND 40 mg; this effect was not considered clinically important.

In another study with intravenous administration of midazolam, EMEND was given as 125 mg on Day 1 and 80 mg/day on Days 2 and 3, and midazolam 2 mg IV was given prior to the administration of the 3-day regimen of EMEND and on Days 4, 8, and 15. EMEND increased the AUC of midazolam by 25% on Day 4 and decreased the AUC of midazolam by 19% on Day 8 relative to the dosing of EMEND on Days 1 through 3. These effects were not considered clinically important. The AUC of midazolam on Day 15 was similar to that observed at baseline.

An additional study was completed with intravenous administration of midazolam and EMEND. Intravenous midazolam 2 mg was given 1 hour after oral administration of a single dose of EMEND 125 mg. The plasma AUC of midazolam was increased by 1.5-fold. Depending on clinical situations (e.g., elderly patients) and degree of monitoring available, dosage adjustment for intravenous midazolam may be necessary when it is coadministered with EMEND for the chemotherapy induced nausea and vomiting indication (125 mg on Day 1 followed by 80 mg on Days 2 and 3).

7.2 Effect of Other Agents on the Pharmacokinetics of Aprepitant

Aprepitant is a substrate for CYP3A4; therefore, coadministration of EMEND with drugs that inhibit CYP3A4 activity may result in increased plasma concentrations of aprepitant. Consequently, concomitant administration of EMEND with strong CYP3A4 inhibitors (e.g., ketoconazole, itraconazole, nefazodone, troleandomycin, clarithromycin, ritonavir, nelfinavir) should be approached with caution. Because moderate CYP3A4 inhibitors (e.g., diltiazem) result in a 2-fold increase in plasma concentrations of aprepitant, concomitant administration should also be approached with caution.

Aprepitant is a substrate for CYP3A4; therefore, coadministration of EMEND with drugs that strongly induce CYP3A4 activity (e.g., rifampin, carbamazepine, phenytoin) may result in reduced plasma concentrations of aprepitant that may result in decreased efficacy of EMEND.

Ketoconazole: When a single 125-mg dose of EMEND was administered on Day 5 of a 10-day regimen of 400 mg/day of ketoconazole, a strong CYP3A4 inhibitor, the AUC of aprepitant increased approximately 5-fold and the mean terminal half-life of aprepitant increased approximately 3-fold. Concomitant administration of EMEND with strong CYP3A4 inhibitors should be approached cautiously.

Rifampin: When a single 375-mg dose of EMEND was administered on Day 9 of a 14-day regimen of 600 mg/day of rifampin, a strong CYP3A4 inducer, the AUC of aprepitant decreased approximately 11-fold and the mean terminal half-life decreased approximately 3-fold.

Coadministration of EMEND with drugs that induce CYP3A4 activity may result in reduced plasma concentrations and decreased efficacy of EMEND.

7.3 Additional Interactions

EMEND is unlikely to interact with drugs that are substrates for the P-glycoprotein transporter, as demonstrated by the lack of interaction of EMEND with digoxin in a clinical drug interaction study.

Diltiazem: In patients with mild to moderate hypertension, administration of aprepitant once daily, as a tablet formulation comparable to 230 mg of the capsule formulation, with diltiazem 120 mg 3 times daily for 5 days, resulted in a 2-fold increase of aprepitant AUC and a simultaneous 1.7-fold increase of diltiazem AUC. These pharmacokinetic effects did not result in clinically meaningful changes in ECG, heart rate or blood pressure beyond those changes induced by diltiazem alone.

Paroxetine: Coadministration of once daily doses of aprepitant, as a tablet formulation comparable to 85 mg or 170 mg of the capsule formulation, with paroxetine 20 mg once daily, resulted in a decrease in AUC by approximately 25% and Cmax by approximately 20% of both aprepitant and paroxetine.

8 USE IN SPECIFIC POPULATIONS

8.1 Pregnancy

Teratogenic effects

Pregnancy Category B: Reproduction studies have been performed in rats at oral doses up to 1000 mg/kg twice daily (plasma AUC0‑24hr of 31.3 mcg•hr/mL, about 1.6 times the human exposure at the recommended dose) and in rabbits at oral doses up to 25 mg/kg/day (plasma AUC0‑24hr of 26.9 mcg•hr/mL, about 1.4 times the human exposure at the recommended dose) and have revealed no evidence of impaired fertility or harm to the fetus due to aprepitant. There are, however, no adequate and well-controlled studies in pregnant women. Because animal reproduction studies are not always predictive of human response, this drug should be used during pregnancy only if clearly needed.

8.3 Nursing Mothers

Aprepitant is excreted in the milk of rats. It is not known whether this drug is excreted in human milk. Because many drugs are excreted in human milk and because of the potential for possible serious adverse reactions in nursing infants from aprepitant and because of the potential for tumorigenicity shown for aprepitant in rodent carcinogenicity studies, a decision should be made whether to discontinue nursing or to discontinue the drug, taking into account the importance of the drug to the mother.

8.4 Pediatric Use

Safety and effectiveness of EMEND in pediatric patients have not been established.

8.5 Geriatric Use

In 2 well-controlled chemotherapy-induced nausea and vomiting clinical studies, of the total number of patients (N=544) treated with EMEND, 31% were 65 and over, while 5% were 75 and over. In well-controlled postoperative nausea and vomiting clinical studies, of the total number of patients (N=1120) treated with EMEND, 7% were 65 and over, while 2% were 75 and over. No overall differences in safety or effectiveness were observed between these subjects and younger subjects. Greater sensitivity of some older individuals cannot be ruled out. Dosage adjustment in the elderly is not necessary.

10 OVERDOSAGE

No specific information is available on the treatment of overdosage.

Drowsiness and headache were reported in one patient who ingested 1440 mg of aprepitant.

In the event of overdose, EMEND should be discontinued and general supportive treatment and monitoring should be provided. Because of the antiemetic activity of aprepitant, drug-induced emesis may not be effective.

Aprepitant cannot be removed by hemodialysis.

11 DESCRIPTION

EMEND (aprepitant) is a substance P/neurokinin 1 (NK1) receptor antagonist, chemically described as 5-[[(2R,3S)-2-[(1R)-1-[3,5-bis(trifluoromethyl)phenyl]ethoxy]-3-(4-fluorophenyl)-4-morpholinyl]methyl]-1,2-dihydro-3H-1,2,4-triazol-3-one.

Its empirical formula is C23H21F7N4O3, and its structural formula is:

Aprepitant is a white to off-white crystalline solid, with a molecular weight of 534.43. It is practically insoluble in water. Aprepitant is sparingly soluble in ethanol and isopropyl acetate and slightly soluble in acetonitrile.

Each capsule of EMEND for oral administration contains either 40 mg, 80 mg, or 125 mg of aprepitant and the following inactive ingredients: sucrose, microcrystalline cellulose, hydroxypropyl cellulose and sodium lauryl sulfate. The capsule shell excipients are gelatin, titanium dioxide, and may contain sodium lauryl sulfate and silicon dioxide. The 40‑mg capsule shell also contains yellow ferric oxide, and the 125‑mg capsule also contains red ferric oxide and yellow ferric oxide.

12 CLINICAL PHARMACOLOGY

12.1 Mechanism of Action

Aprepitant is a selective high-affinity antagonist of human substance P/neurokinin 1 (NK1) receptors. Aprepitant has little or no affinity for serotonin (5-HT3), dopamine, and corticosteroid receptors, the targets of existing therapies for chemotherapy-induced nausea and vomiting (CINV) and postoperative nausea and vomiting (PONV).

Aprepitant has been shown in animal models to inhibit emesis induced by cytotoxic chemotherapeutic agents, such as cisplatin, via central actions. Animal and human Positron Emission Tomography (PET) studies with aprepitant have shown that it crosses the blood brain barrier and occupies brain NK1 receptors. Animal and human studies show that aprepitant augments the antiemetic activity of the 5-HT3-receptor antagonist ondansetron and the corticosteroid dexamethasone and inhibits both the acute and delayed phases of cisplatin-induced emesis.

12.2 Pharmacodynamics

NK1 Receptor Occupancy

In two single-blind, multiple-dose, randomized, and placebo control studies, healthy young men received oral aprepitant doses of 10 mg (N=2), 30 mg (N=3), 100 mg (N=3) or 300 mg (N=5) once daily for 14 days with 2 or 3 subjects on placebo. Both plasma aprepitant concentration and NK1 receptor occupancy in the corpus striatum by positron emission tomography were evaluated, at predose and 24 hours after the last dose. At aprepitant plasma concentrations of ~10 ng/mL and ~100 ng/mL, the NK1 receptor occupancies were ~50% and ~90%, respectively. The oral aprepitant regimen for CINV produces mean trough plasma aprepitant concentrations >500 ng/mL, which would be expected to, based on the fitted curve with the Hill equation, result in >95% brain NK1 receptor occupancy. However, the receptor occupancy for either CINV or PONV dosing regimen has not been determined. In addition, the relationship between NK1 receptor occupancy and the clinical efficacy of aprepitant has not been established.

Cardiac Electrophysiology

In a randomized, double-blind, positive-controlled, thorough QTc study, a single 200-mg dose of fosaprepitant had no effect on the QTc interval. QT prolongation with the oral dosing regimens for CINV and PONV are not expected.

12.3 Pharmacokinetics

Absorption

Following oral administration of a single 40 mg dose of EMEND in the fasted state, mean area under the plasma concentration-time curve (AUC0‑∞) was 7.8 mcg•hr/mL and mean peak plasma concentration (Cmax) was 0.7 mcg/mL, occurring at approximately 3 hours postdose (Tmax). The absolute bioavailability at the 40‑mg dose has not been determined.

Following oral administration of a single 125-mg dose of EMEND on Day 1 and 80 mg once daily on Days 2 and 3, the AUC0-24hr was approximately 19.6 mcg•hr/mL and 21.2 mcg•hr/mL on Day 1 and Day 3, respectively. The Cmax of 1.6 mcg/mL and 1.4 mcg/mL were reached in approximately 4 hours (Tmax) on Day 1 and Day 3, respectively. At the dose range of 80-125 mg, the mean absolute oral bioavailability of aprepitant is approximately 60 to 65%. Oral administration of the capsule with a standard high-fat breakfast had no clinically meaningful effect on the bioavailability of aprepitant.

The pharmacokinetics of aprepitant are non-linear across the clinical dose range. In healthy young adults, the increase in AUC0‑∞ was 26% greater than dose proportional between 80‑mg and 125‑mg single doses administered in the fed state.

Distribution

Aprepitant is greater than 95% bound to plasma proteins. The mean apparent volume of distribution at steady state (Vdss) is approximately 70 L in humans.

Aprepitant crosses the placenta in rats and rabbits and crosses the blood brain barrier in humans [see Clinical Pharmacology (12.1)].

Metabolism

Aprepitant undergoes extensive metabolism. In vitro studies using human liver microsomes indicate that aprepitant is metabolized primarily by CYP3A4 with minor metabolism by CYP1A2 and CYP2C19. Metabolism is largely via oxidation at the morpholine ring and its side chains. No metabolism by CYP2D6, CYP2C9, or CYP2E1 was detected. In healthy young adults, aprepitant accounts for approximately 24% of the radioactivity in plasma over 72 hours following a single oral 300-mg dose of [^14C]-aprepitant, indicating a substantial presence of metabolites in the plasma. Seven metabolites of aprepitant, which are only weakly active, have been identified in human plasma.

Excretion

Following administration of a single IV 100-mg dose of [^14C]-aprepitant prodrug to healthy subjects, 57% of the radioactivity was recovered in urine and 45% in feces. A study was not conducted with radiolabeled capsule formulation. The results after oral administration may differ.

Aprepitant is eliminated primarily by metabolism; aprepitant is not renally excreted. The apparent plasma clearance of aprepitant ranged from approximately 62 to 90 mL/min. The apparent terminal half-life ranged from approximately 9 to 13 hours.

Special Populations

Gender

Following oral administration of a single 125-mg dose of EMEND, no difference in AUC0‑24hr was observed between males and females. The Cmax for aprepitant is 16% higher in females as compared with males. The half-life of aprepitant is 25% lower in females as compared with males and Tmax occurs at approximately the same time. These differences are not considered clinically meaningful. No dosage adjustment for EMEND is necessary based on gender.

Geriatric

Following oral administration of a single 125-mg dose of EMEND on Day 1 and 80 mg once daily on Days 2 through 5, the AUC0‑24hr of aprepitant was 21% higher on Day 1 and 36% higher on Day 5 in elderly (≥65 years) relative to younger adults. The Cmax was 10% higher on Day 1 and 24% higher on Day 5 in elderly relative to younger adults. These differences are not considered clinically meaningful. No dosage adjustment for EMEND is necessary in elderly patients.

Pediatric

EMEND has not been evaluated in patients below 18 years of age.

Race

Following oral administration of a single 125-mg dose of EMEND, the AUC0-24hr is approximately 25% and 29% higher in Hispanics as compared with Whites and Blacks, respectively. The Cmax is 22% and 31% higher in Hispanics as compared with Whites and Blacks, respectively. These differences are not considered clinically meaningful. There was no difference in AUC0-24hr or Cmax between Whites and Blacks. No dosage adjustment for EMEND is necessary based on race.

Hepatic Insufficiency

Following administration of a single 125‑mg dose of EMEND on Day 1 and 80 mg once daily on Days 2 and 3 to patients with mild hepatic impairment (Child-Pugh score 5 to 6), the AUC0-24hr of aprepitant was 11% lower on Day 1 and 36% lower on Day 3, as compared with healthy subjects given the same regimen. In patients with moderate hepatic impairment (Child-Pugh score 7 to 9), the AUC0-24hr of aprepitant was 10% higher on Day 1 and 18% higher on Day 3, as compared with healthy subjects given the same regimen. These differences in AUC0‑24hr are not considered clinically meaningful; therefore, no dosage adjustment for EMEND is necessary in patients with mild to moderate hepatic impairment.

There are no clinical or pharmacokinetic data in patients with severe hepatic impairment (Child-Pugh score >9) [see Warnings and Precautions (5.4)].

Renal Insufficiency

A single 240-mg dose of EMEND was administered to patients with severe renal impairment (CrCl<30 mL/min) and to patients with end stage renal disease (ESRD) requiring hemodialysis.

In patients with severe renal impairment, the AUC0-∞ of total aprepitant (unbound and protein bound) decreased by 21% and Cmax decreased by 32%, relative to healthy subjects. In patients with ESRD undergoing hemodialysis, the AUC0‑∞ of total aprepitant decreased by 42% and Cmax decreased by 32%. Due to modest decreases in protein binding of aprepitant in patients with renal disease, the AUC of pharmacologically active unbound drug was not significantly affected in patients with renal impairment compared with healthy subjects. Hemodialysis conducted 4 or 48 hours after dosing had no significant effect on the pharmacokinetics of aprepitant; less than 0.2% of the dose was recovered in the dialysate.

No dosage adjustment for EMEND is necessary for patients with renal impairment or for patients with ESRD undergoing hemodialysis.

13 NONCLINICAL TOXICOLOGY

13.1 Carcinogenesis, Mutagenesis, Impairment of Fertility

Carcinogenicity studies were conducted in Sprague-Dawley rats and in CD-1 mice for 2 years. In the rat carcinogenicity studies, animals were treated with oral doses ranging from 0.05 to 1000 mg/kg twice daily. The highest dose produced a systemic exposure to aprepitant (plasma AUC0‑24hr) of 0.7 to 1.6 times the human exposure (AUC0‑24hr = 19.6 mcg•hr/mL) at the recommended dose of 125 mg/day. Treatment with aprepitant at doses of 5 to 1000 mg/kg twice daily caused an increase in the incidences of thyroid follicular cell adenomas and carcinomas in male rats. In female rats, it produced hepatocellular adenomas at 5 to 1000 mg/kg twice daily and hepatocellular carcinomas and thyroid follicular cell adenomas at 125 to 1000 mg/kg twice daily. In the mouse carcinogenicity studies, the animals were treated with oral doses ranging from 2.5 to 2000 mg/kg/day. The highest dose produced a systemic exposure of about 2.8 to 3.6 times the human exposure at the recommended dose. Treatment with aprepitant produced skin fibrosarcomas at 125 and 500 mg/kg/day doses in male mice.

Aprepitant was not genotoxic in the Ames test, the human lymphoblastoid cell (TK6) mutagenesis test, the rat hepatocyte DNA strand break test, the Chinese hamster ovary (CHO) cell chromosome aberration test and the mouse micronucleus test.

Aprepitant did not affect the fertility or general reproductive performance of male or female rats at doses up to the maximum feasible dose of 1000 mg/kg twice daily (providing exposure in male rats lower than the exposure at the recommended human dose and exposure in female rats at about 1.6 times the human exposure).

14 CLINICAL STUDIES

14.1 Prevention of Chemotherapy Induced Nausea and Vomiting (CINV)

Oral administration of EMEND in combination with ondansetron and dexamethasone (aprepitant regimen) has been shown to prevent acute and delayed nausea and vomiting associated with highly emetogenic chemotherapy including high-dose cisplatin, and nausea and vomiting associated with moderately emetogenic chemotherapy.

Highly Emetogenic Chemotherapy (HEC)

In 2 multicenter, randomized, parallel, double-blind, controlled clinical studies, the aprepitant regimen (see Table 6) was compared with standard therapy in patients receiving a chemotherapy regimen that included cisplatin >50 mg/m^2 (mean cisplatin dose = 80.2 mg/m^2). Of the 550 patients who were randomized to receive the aprepitant regimen, 42% were women, 58% men, 59% White, 3% Asian, 5% Black, 12% Hispanic American, and 21% Multi-Racial. The aprepitant-treated patients in these clinical studies ranged from 14 to 84 years of age, with a mean age of 56 years. 170 patients were 65 years or older, with 29 patients being 75 years or older.

Patients (N = 1105) were randomized to either the aprepitant regimen (N = 550) or standard therapy (N = 555). The treatment regimens are defined in Table 5.

Table 5: Treatment Regimens in Highly Emetogenic Chemotherapy Trials
Treatment Regimen | Day 1 | Days 2 to 4
Aprepitant | Aprepitant 125 mg PO Dexamethasone 12 mg PO Ondansetron 32 mg I.V. | Aprepitant 80 mg PO Daily (Days 2 and 3 only) Dexamethasone 8 mg PO Daily (morning)
Standard Therapy | Dexamethasone 20 mg PO Ondansetron 32 mg I.V. | Dexamethasone 8 mg PO Daily (morning) Dexamethasone 8 mg PO Daily (evening)
Aprepitant placebo and dexamethasone placebo were used to maintain blinding.

During these studies 95% of the patients in the aprepitant group received a concomitant chemotherapeutic agent in addition to protocol-mandated cisplatin. The most common chemotherapeutic agents and the number of aprepitant patients exposed follows: etoposide (106), fluorouracil (100), gemcitabine (89), vinorelbine (82), paclitaxel (52), cyclophosphamide (50), doxorubicin (38), docetaxel (11).

The antiemetic activity of EMEND was evaluated during the acute phase (0 to 24 hours post-cisplatin treatment), the delayed phase (25 to 120 hours post-cisplatin treatment) and overall (0 to 120 hours post-cisplatin treatment) in Cycle 1. Efficacy was based on evaluation of the following endpoints:

Primary endpoint:

- complete response (defined as no emetic episodes and no use of rescue therapy)

Other prespecified endpoints:

- complete protection (defined as no emetic episodes, no use of rescue therapy, and a maximum nausea visual analogue scale [VAS] score <25 mm on a 0 to 100 mm scale)
- no emesis (defined as no emetic episodes regardless of use of rescue therapy)
- no nausea (maximum VAS <5 mm on a 0 to 100 mm scale)
- no significant nausea (maximum VAS <25 mm on a 0 to 100 mm scale)

A summary of the key study results from each individual study analysis is shown in Table 6 and in Table 7.

Table 6: Percent of Patients Receiving Highly Emetogenic Chemotherapy Responding by Treatment Group and Phase for Study 1 — Cycle 1
ENDPOINTS | Aprepitant Regimen (N = 260) [N: Number of patients (older than 18 years of age) who received cisplatin, study drug, and had at least one post-treatment efficacy evaluation.] % | Standard Therapy (N = 261) % | p-Value
PRIMARY ENDPOINT
Complete Response
Overall [Overall: 0 to 120 hours post-cisplatin treatment.] | 73 | 52 | <0.001
OTHER PRESPECIFIED ENDPOINTS
Complete Response
Acute phase [Acute phase: 0 to 24 hours post-cisplatin treatment.] Delayed phase [Delayed phase: 25 to 120 hours post-cisplatin treatment.] | 89 75 | 78 56 | <0.001 <0.001
Complete Protection
Overall Acute phase Delayed phase | 63 85 66 | 49 75 52 | 0.001 NS [Not statistically significant when adjusted for multiple comparisons.] <0.001
No Emesis
Overall Acute phase Delayed phase | 78 90 81 | 55 79 59 | <0.001 0.001 <0.001
No Nausea
Overall Delayed phase | 48 51 | 44 48 | NS [Not statistically significant.] NS
No Significant Nausea
Overall Delayed phase | 73 75 | 66 69 | NS NS
Visual analogue scale (VAS) score range: 0 mm = no nausea; 100 mm = nausea as bad as it could be.

Table 7: Percent of Patients Receiving Highly Emetogenic Chemotherapy Responding by Treatment Group and Phase for Study 2 — Cycle 1
ENDPOINTS | Aprepitant Regimen (N = 261) [N: Number of patients (older than 18 years of age) who received cisplatin, study drug, and had at least one post-treatment efficacy evaluation.] % | Standard Therapy (N = 263) % | p-Value
PRIMARY ENDPOINT
Complete Response
Overall [Overall: 0 to 120 hours post-cisplatin treatment.] | 63 | 43 | <0.001
OTHER PRESPECIFIED ENDPOINTS
Complete Response
Acute phase [Acute phase: 0 to 24 hours post-cisplatin treatment.] Delayed phase [Delayed phase: 25 to 120 hours post-cisplatin treatment.] | 83 68 | 68 47 | <0.001 <0.001
Complete Protection
Overall Acute phase Delayed phase | 56 80 61 | 41 65 44 | <0.001 <0.001 <0.001
No Emesis
Overall Acute phase Delayed phase | 66 84 72 | 44 69 48 | <0.001 <0.001 <0.001
No Nausea
Overall Delayed phase | 49 53 | 39 40 | NS [Not statistically significant when adjusted for multiple comparisons.] NS
No Significant Nausea
Overall Delayed phase | 71 73 | 64 65 | NS [Not statistically significant.] NS
Visual analogue scale (VAS) score range: 0 mm = no nausea; 100 mm = nausea as bad as it could be.

In both studies, a statistically significantly higher proportion of patients receiving the aprepitant regimen in Cycle 1 had a complete response in the overall phase (primary endpoint), compared with patients receiving standard therapy. A statistically significant difference in complete response in favor of the aprepitant regimen was also observed when the acute phase and the delayed phase were analyzed separately.

In both studies, the estimated time to first emesis after initiation of cisplatin treatment was longer with the aprepitant regimen, and the incidence of first emesis was reduced in the aprepitant regimen group compared with standard therapy group as depicted in the Kaplan-Meier curves in Figure 1.

Figure 1: Percent of Patients Receiving Highly Emetogenic Chemotherapy Who Remain Emesis Free Over Time — Cycle 1

Patient-Reported Outcomes: The impact of nausea and vomiting on patients’ daily lives was assessed in Cycle 1 of both Phase III studies using the Functional Living Index–Emesis (FLIE), a validated nausea- and vomiting-specific patient-reported outcome measure. Minimal or no impact of nausea and vomiting on patients’ daily lives is defined as a FLIE total score >108. In each of the 2 studies, a higher proportion of patients receiving the aprepitant regimen reported minimal or no impact of nausea and vomiting on daily life (Study 1: 74% versus 64%; Study 2: 75% versus 64%).

Multiple-Cycle Extension: In the same 2 clinical studies, patients continued into the Multiple-Cycle extension for up to 5 additional cycles of chemotherapy. The proportion of patients with no emesis and no significant nausea by treatment group at each cycle is depicted in Figure 2. Antiemetic effectiveness for the patients receiving the aprepitant regimen is maintained throughout repeat cycles for those patients continuing in each of the multiple cycles.

Figure 2: Proportion of Patients Receiving Highly Emetogenic Chemotherapy with No Emesis and No Significant Nausea by Treatment Group and Cycle

Moderately Emetogenic Chemotherapy (MEC)

In a multicenter, randomized, double-blind, parallel-group, clinical study in breast cancer patients, the aprepitant regimen (see Table 9) was compared with a standard of care therapy in patients receiving a moderately emetogenic chemotherapy regimen that included cyclophosphamide 750-1500 mg/m^2; or cyclophosphamide 500-1500 mg/m^2 and doxorubicin (≤60 mg/m^2) or epirubicin (≤100 mg/m^2).

In this study, the most common combinations were cyclophosphamide + doxorubicin (60.6%); and cyclophosphamide + epirubicin + fluorouracil (21.6%).

Of the 438 patients who were randomized to receive the aprepitant regimen, 99.5% were women. Of these, approximately 80% were White, 8% Black, 8% Asian, 4% Hispanic, and <1% Other. The aprepitant-treated patients in this clinical study ranged from 25 to 78 years of age, with a mean age of 53 years; 70 patients were 65 years or older, with 12 patients being over 74 years.

Patients (N = 866) were randomized to either the aprepitant regimen (N = 438) or standard therapy (N = 428). The treatment regimens are defined in Table 8.

Table 8: Treatment Regimens in Moderately Emetogenic Chemotherapy Trials
Treatment Regimen | Day 1 | Days 2 to 3
Aprepitant | Aprepitant 125 mg PO [1 hour prior to chemotherapy.] Dexamethasone 12 mg PO [30 minutes prior to chemotherapy.] Ondansetron 8 mg PO x 2 doses [30 to 60 minutes prior to chemotherapy and 8 hours after first ondansetron dose.] | Aprepitant 80 mg PO Daily
Standard Therapy | Dexamethasone 20 mg PO Ondansetron 8 mg PO x 2 doses | Ondansetron 8 mg PO Daily (every 12 hours)
Aprepitant placebo and dexamethasone placebo were used to maintain blinding.

The antiemetic activity of EMEND was evaluated based on the following endpoints:

Primary endpoint:

Complete response (defined as no emetic episodes and no use of rescue therapy) in the overall phase (0 to 120 hours post-chemotherapy)

Other prespecified endpoints:

- no emesis (defined as no emetic episodes regardless of use of rescue therapy)
- no nausea (maximum VAS <5 mm on a 0 to 100 mm scale)
- no significant nausea (maximum VAS <25 mm on a 0 to 100 mm scale)
- complete protection (defined as no emetic episodes, no use of rescue therapy, and a maximum nausea visual analogue scale [VAS] score <25 mm on a 0 to 100 mm scale)
- complete response during the acute and delayed phases.

A summary of the key results from this study is shown in Table 9.

Table 9: Percent of Patients Receiving Moderately Emetogenic Chemotherapy Responding by Treatment Group and Phase — Cycle 1
ENDPOINTS | Aprepitant Regimen (N = 433) [N: Number of patients included in the primary analysis of complete response.] % | Standard Therapy (N = 424) % | p-Value
PRIMARY ENDPOINT [Overall: 0 to 120 hours post-chemotherapy treatment.]
Complete Response | 51 | 42 | 0.015
OTHER PRESPECIFIED ENDPOINTS
No Emesis | 76 | 59 | NS [NS when adjusted for prespecified multiple comparisons rule; unadjusted p-value <0.001.]
No Nausea | 33 | 33 | NS
No Significant Nausea | 61 | 56 | NS
No Rescue Therapy | 59 | 56 | NS
Complete Protection | 43 | 37 | NS

In this study, a statistically significantly (p=0.015) higher proportion of patients receiving the aprepitant regimen (51%) in Cycle 1 had a complete response (primary endpoint) during the overall phase compared with patients receiving standard therapy (42%). The difference between treatment groups was primarily driven by the “No Emesis Endpoint”, a principal component of this composite primary endpoint. In addition, a higher proportion of patients receiving the aprepitant regimen in Cycle 1 had a complete response during the acute (0-24 hours) and delayed (25-120 hours) phases compared with patients receiving standard therapy; however, the treatment group differences failed to reach statistical significance, after multiplicity adjustments.

Patient-Reported Outcomes: In a phase III study in patients receiving moderately emetogenic chemotherapy, the impact of nausea and vomiting on patients’ daily lives was assessed in Cycle 1 using the FLIE. A higher proportion of patients receiving the aprepitant regimen reported minimal or no impact on daily life (64% versus 56%). This difference between treatment groups was primarily driven by the “No Vomiting Domain” of this composite endpoint.

Multiple-Cycle Extension: Patients receiving moderately emetogenic chemotherapy were permitted to continue into the Multiple-Cycle extension of the study for up to 3 additional cycles of chemotherapy. Antiemetic effect for patients receiving the aprepitant regimen is maintained during all cycles.

Postmarketing Trial: In a postmarketing, multicenter, randomized, double-blind, parallel-group, clinical study in 848 cancer patients, the aprepitant regimen (N = 430) was compared with a standard of care therapy (N = 418) in patients receiving a moderately emetogenic chemotherapy regimen that included any IV dose of oxaliplatin, carboplatin, epirubicin, idarubicin, ifosfamide, irinotecan, daunorubicin, doxorubicin; cyclophosphamide IV (<1500 mg/m^2); or cytarabine IV (>1 g/m^2).

Of the 430 patients who were randomized to receive the aprepitant regimen, approximately 76% were women and 24% were men. The distribution by race was 67% White, 6% Black or African American, 11% Asian, and 12% multiracial. Classified by ethnicity, 36% were Hispanic and 64% were non-Hispanic. The aprepitant-treated patients in this clinical study ranged from 22 to 85 years of age, with a mean age of 57 years; approximately 59% of the patients were 55 years or older with 32 patients being over 74 years. Patients receiving the aprepitant regimen were receiving chemotherapy for a variety of tumor types including 50% with breast cancer, 21% with gastrointestinal cancers including colorectal cancer, 13% with lung cancer and 6% with gynecological cancers.

The antiemetic activity of EMEND was evaluated based on no vomiting (with or without rescue therapy) in the overall period (0 to 120 hours post-chemotherapy) and complete response (defined as no vomiting and no use of rescue therapy) in the overall period.

A summary of the key results from this study is shown in Table 10.

Table 10: Percent of Patients Receiving Moderately Emetogenic Chemotherapy Responding by Treatment Group for Study 2 — Cycle 1
ENDPOINTS | Aprepitant Regimen; (N = 430) [N = Number of patients who received chemotherapy treatment, study drug, and had at least one post-treatment efficacy evaluation.]; % | Standard Therapy; (N = 418); % | p-Value
No Vomiting Overall | 76 | 62 | <0.0001
Complete Response Overall | 69 | 56 | 0.0003

In this study, a statistically significantly higher proportion of patients receiving the aprepitant regimen (76%) in Cycle 1 had no vomiting during the overall phase compared with patients receiving standard therapy (62%). In addition, a higher proportion of patients receiving the aprepitant regimen (69%) in Cycle 1 had a complete response in the overall phase (0-120 hours) compared with patients receiving standard therapy (56%). In the acute phase (0 to 24 hours following initiation of chemotherapy), a higher proportion of patients receiving aprepitant compared to patients receiving standard therapy were observed to have no vomiting (92% and 84%, respectively) and complete response (89% and 80%, respectively). In the delayed phase (25 to 120 hours following initiation of chemotherapy), a higher proportion of patients receiving aprepitant compared to patients receiving standard therapy were observed to have no vomiting (78% and 67%, respectively) and complete response (71% and 61%, respectively).

In a subgroup analysis by tumor type, a numerically higher proportion of patients receiving aprepitant were observed to have no vomiting and complete response compared to patients receiving standard therapy. For gender, the difference in complete response rates between the aprepitant and standard regimen groups was 14% in females (64.5% and 50.3%, respectively) and 4% in males (82.2% and 78.2%, respectively) during the overall phase. A similar difference for gender was observed for the no vomiting endpoint.

14.2 Prevention of Postoperative Nausea and Vomiting (PONV)

In two multicenter, randomized, double-blind, active comparator-controlled, parallel-group clinical studies (PONV Studies 1 and 2), aprepitant was compared with ondansetron for the prevention of postoperative nausea and vomiting in 1658 patients undergoing open abdominal surgery. Patients were randomized to receive 40 mg aprepitant, 125 mg aprepitant, or 4 mg ondansetron. Aprepitant was given orally with 50 mL of water 1 to 3 hours before anesthesia. Ondansetron was given intravenously immediately before induction of anesthesia. A comparison between the 125 mg dose and the 40 mg dose did not demonstrate any additional clinical benefit. The remainder of this section will focus on the results in the 40 mg aprepitant dose recommended for PONV.

Of the 564 patients who received 40 mg aprepitant, 92% were women and 8% were men; of these, 58% were White, 13% Hispanic American, 7% Multi-Racial, 14% Black, 6% Asian, and 2% Other. The age of patients treated with 40 mg aprepitant ranged from 19 to 84 years, with a mean age of 46.1 years. 46 patients were 65 years or older, with 13 patients being 75 years or older.

The antiemetic activity of EMEND was evaluated during the 0 to 48 hour period following the end of surgery. The two pivotal studies were of similar design; however, they differed in terms of study hypothesis, efficacy analyses and geographic location. PONV Study 1 was a multinational study including the U.S., whereas, PONV Study 2 was conducted entirely in the U.S.

Efficacy measures in PONV Study 1 included:

- no emesis (defined as no emetic episodes regardless of use of rescue therapy) in the 0 to 24 hours following the end of surgery (primary)
- complete response (defined as no emetic episodes and no use of rescue therapy) in the 0 to 24 hours following the end of surgery (primary)
- no emesis (defined as no emetic episodes regardless of use of rescue therapy) in the 0 to 48 hours following the end of surgery (secondary)
- time to first use of rescue medication in the 0 to 24 hours following the end of surgery (exploratory)
- time to first emesis in the 0 to 48 hours following the end of surgery (exploratory).

A closed testing procedure was applied to control the type I error for the primary endpoints.

The results of the primary and secondary endpoints for 40 mg aprepitant and 4 mg ondansetron are described in Table 11:

Table 11: PONV Study 1 – Response Rates for Select Efficacy Endpoints (Modified-Intention-to-Treat Population)
Treatment | n/m (%) | Aprepitant vs Ondansetron
Treatment | n/m (%) | Δ | Odds ratio [Estimated odds ratio for Aprepitant versus Ondansetron. A value of >1 favors Aprepitant over Ondansetron.] | Analysis
Primary Endpoints
No Vomiting 0 to 24 hours (Superiority)
(no emetic episodes)
Aprepitant 40 mg | 246/293 (84.0) | 12.6% | 2.1 | P<0.001 [P-value of two-sided test <0.05.]
Ondansetron | 200/280 (71.4)
Complete Response (Non-inferiority: If LB [LB= lower bound of 1-sided 97.5% confidence interval for the odds ratio.] >0.65)
(no emesis and no rescue therapy, 0 to 24 hours)
Aprepitant 40 mg | 187/293 (63.8) | 8.8% | 1.4 | LB=1.02
Ondansetron | 154/280 (55.0)
Complete Response (Superiority: If LB >1.0)
(no emesis and no rescue therapy, 0 to 24 hours)
Aprepitant 40 mg | 187/293 (63.8) | 8.8% | 1.4 | LB=1.02 [Based on the prespecified fixed sequence multiplicity strategy, Aprepitant 40 mg was not superior to Ondansetron.]
Ondansetron | 154/280 (55.0)
Secondary Endpoint
No Vomiting 0 to 48 (Superiority)
(no emetic episodes)
Aprepitant 40 mg | 238/292 (81.5) | 15.2% | 2.3 | P<0.001
Ondansetron | 185/279 (66.3)
n/m = Number of responders/number of patients in analysis.
Δ Difference (%): Aprepitant 40 mg minus Ondansetron.

The use of aprepitant did not affect the time to first use of rescue medication when compared to ondansetron. However, compared to the ondansetron group, use of aprepitant delayed the time to first vomiting, as depicted in Figure 3.

Figure 3: Percent of Patients Who Remain Emesis Free During the 48 Hours Following End of Surgery

Efficacy measures in PONV Study 2 included:

- complete response (defined as no emetic episodes and no use of rescue therapy) in the 0 to 24 hours following the end of surgery (primary)
- no emesis (defined as no emetic episodes regardless of use of rescue therapy) in the 0 to 24 hours following the end of surgery (secondary)
- no use of rescue therapy in the 0 to 24 hours following the end of surgery (secondary)
- no emesis (defined as no emetic episodes regardless of use of rescue therapy) in the 0 to 48 hours following the end of surgery (secondary).

PONV Study 2 failed to satisfy its primary hypothesis that aprepitant is superior to ondansetron in the prevention of PONV as measured by the proportion of patients with complete response in the 24 hours following end of surgery.

The study demonstrated that both dose levels of aprepitant had a clinically meaningful effect with respect to the secondary endpoint “no vomiting” during the first 24 hours after surgery and showed that the use of 40 mg aprepitant was associated with a 16% improvement over ondansetron for the no vomiting endpoint.

Table 12: PONV Study 2 (Modified-Intention-to-Treat Population)
Treatment | n/m (%) | Aprepitant vs Ondansetron
Treatment | n/m (%) | Δ | Odds ratio [Estimated odds ratio: Aprepitant 40 mg versus Ondansetron.] | p-Value
Primary Endpoint
Complete Response
(no emesis and no rescue therapy, 0 to 24 hours)
Aprepitant 40 mg | 111/248 (44.8) | 2.5% | 1.1 | 0.61
Ondansetron | 104/246 (42.3)
Secondary Endpoints
No Vomiting
(no emetic episodes, 0 to 24 hours)
Aprepitant 40 mg | 223/248 (89.9) | 16.3% | 3.2 | <0.001 [Not statistically significant after pre-specified multiplicity adjustment.]
Ondansetron | 181/246 (73.6)
No Use of Rescue Medication
(for established emesis or nausea, 0 to 24 hours)
Aprepitant 40 mg | 112/248 (45.2) | -0.7% | 1.0 | 0.83
Ondansetron | 113/246 (45.9)
No Vomiting 0 to 48 (Superiority)
(no emetic episodes, 0 to 48 hours)
Aprepitant 40 mg | 209/247 (84.6) | 17.7% | 2.7 | <0.001
Ondansetron | 164/245 (66.9)
n/m = Number of responders/number of patients in analysis.
Δ Difference (%): Aprepitant 40 mg minus Ondansetron.

16 HOW SUPPLIED/STORAGE AND HANDLING

No. 6741 — 40 mg capsules: Opaque, hard gelatin capsule with white body and mustard yellow cap with “464” and “40 mg” printed radially in black ink on the body. They are supplied as follows:

NDC 42254-160-01 unit-of-use package of 1

Storage

Store at 20-25°C (68-77°F) [see USP Controlled Room Temperature].

Merck Sharp & Dohme Corp., a subsidiary of
MERCK & CO., INC., Whitehouse Station, NJ 08889, USA

9988902

U.S. Patent Nos.: 5,145,684; 5,719,147; 6,048,859; 6,096,742; 6,235,735

17 PATIENT COUNSELING INFORMATION

[See FDA-Approved Patient Labeling.]

17.1 Instructions

Physicians should instruct their patients to read the patient package insert before starting therapy with EMEND and to reread it each time the prescription is renewed.

Patients should be instructed to take EMEND only as prescribed. For the prevention of chemotherapy induced nausea and vomiting (CINV), patients should be advised to take their first dose (125 mg) of EMEND 1 hour prior to chemotherapy treatment. For the prevention of postoperative nausea and vomiting (PONV), patients should receive their medication (40 mg capsule of EMEND) within 3 hours prior to induction of anesthesia.

Allergic reactions, which may be serious, and may include hives, rash and itching and cause difficulty in breathing or swallowing, have been reported in general use with EMEND. Physicians should instruct their patients to stop taking EMEND and call their doctor right away if they experience an allergic reaction. In addition, severe skin reactions may occur rarely.

EMEND may interact with some drugs including chemotherapy; therefore, patients should be advised to report to their doctor the use of any other prescription, non-prescription medication or herbal products.

Patients on chronic warfarin therapy should be instructed to have their clotting status closely monitored in the 2-week period, particularly at 7 to 10 days, following initiation of the 3-day regimen of EMEND 125 mg/80 mg with each chemotherapy cycle, or following administration of a single 40 mg dose of EMEND for the prevention of postoperative nausea and vomiting.

Administration of EMEND may reduce the efficacy of hormonal contraceptives. Patients should be advised to use alternative or back-up methods of contraception during treatment with EMEND and for 1 month following the last dose of EMEND.

FDA-Approved Patient Labeling

Patient Information
EMEND® (EE mend)
(aprepitant)
Capsules

Read the Patient Information that comes with EMEND before you start taking it and each time you refill your prescription. There may be new information. This leaflet does not take the place of talking with your doctor about your medical condition or treatment.

What is EMEND?

EMEND is a prescription medicine used in adults to prevent nausea and vomiting:

- caused by certain anti-cancer (chemotherapy) medicines. When used for this purpose, EMEND is always used with other medicines.
- after surgery.

EMEND is not used to treat nausea and vomiting that you already have.

EMEND should not be used continuously for a long time (chronic use).

It is not known if EMEND is safe and effective in children.

Who should not take EMEND?

Do not take EMEND if you:

- are taking any of the following medicines:
  - ORAP® (pimozide)
  - SELDANE® (terfenadine)
  - HISMANAL® (astemizole)
  - PROPULSID® (cisapride)

Taking EMEND with any of these medicines could cause serious or life-threatening problems.

- are allergic to any of the ingredients in EMEND. See the end of this leaflet for a list of all the ingredients in EMEND.

What should I tell my doctor before and during treatment with EMEND?

Before you take EMEND, tell your doctor if you:

- have liver problems
- are pregnant or plan to become pregnant. It is not known if EMEND can harm your unborn baby.
  Women who use birth control medicines containing hormones to prevent pregnancy (birth control pills, skin patches, implants, and certain IUDs) should also use a back-up method of birth control during treatment with EMEND and for up to 1 month after using EMEND to prevent pregnancy.
- are breast-feeding. It is not known if EMEND passes into your milk and if it can harm your baby.

Tell your doctor about all the medicines you are taking or plan to take, including prescription and non-prescription medicines, vitamins, and herbal supplements.

EMEND may cause serious life-threatening reactions if used with certain medicines. See the section “Who should not take EMEND?"

EMEND may affect how other medicines work, and other medicines may affect how EMEND works. Ask your doctor or pharmacist before you take any new medicine. They can tell you if it is safe to take the medicine with EMEND.

Know the medicines you take. Keep a list of them to show your doctor or pharmacist when you get a new medicine.

How should I take EMEND?

- Take EMEND exactly as prescribed.
- If you take too much EMEND, call your doctor, local emergency department or poison control center right away.
- If you are receiving cancer chemotherapy, EMEND is taken as 3 doses over 3 days - starting on the day you have chemotherapy, and the two days after chemotherapy. There are two ways that your doctor may prescribe EMEND for you:

1. Capsules of EMEND by mouth for all 3 doses:
  - You should get a package that has three capsules of EMEND.
  - Day 1 (Day of chemotherapy): Take one 125-mg capsule of EMEND (white and pink) by mouth 1 hour before you start your chemotherapy treatment.
  - Day 2 and Day 3 (the two days after chemotherapy): Take one 80-mg capsule of EMEND (white) by mouth, each morning for the 2 days after your chemotherapy treatment.
    Or
2. Intravenous (IV) injection into a vein the first day, then capsules by mouth on the two days after chemotherapy:
  - Day 1 (Day of chemotherapy): EMEND will be given to you by intravenous (IV) injection in your vein 30 minutes before you start your chemotherapy treatment.
  - You should get a package that has two capsules of EMEND.
  - Day 2 and Day 3 (the two days after chemotherapy): Take one 80-mg capsule of EMEND (white) by mouth, each morning for the 2 days after your chemotherapy treatment.

- If you are receiving chemotherapy, EMEND may be taken with or without food.
- If you are having surgery:
  - Your doctor will prescribe a 40-mg capsule of EMEND for you before surgery. You take EMEND within three hours before surgery.
  - Follow your doctor’s instructions about restrictions on eating and drinking before surgery.
- If you take the blood thinner medicine warfarin sodium (COUMADIN®, JANTOVEN®), your doctor may do blood tests after you take EMEND to check your blood clotting.

What are the possible side effects of EMEND?

EMEND may cause serious side effects, including:

- Serious allergic reactions. Allergic reactions can happen with EMEND and may be serious. Stop taking EMEND and call your doctor right away if you have any of these signs or symptoms of an allergic reaction:
  - hives
  - rash
  - itching
  - trouble breathing or swallowing.
- Severe skin reactions may occur rarely.

In people taking EMEND to prevent nausea and vomiting caused by chemotherapy, the most common side effects of EMEND include:

- tiredness
- nausea
- hiccups
- constipation
- diarrhea
- loss of appetite
- headache
- hair loss

In people taking EMEND to prevent nausea and vomiting after surgery, the most common side effects are:

- constipation
- nausea
- itch
- fever
- low blood pressure
- headache

Tell your doctor if you have any side effect that bothers you or that does not go away. These are not all of the possible side effects of EMEND. For more information ask your doctor or pharmacist.

Call your doctor for medical advice about side effects. You may report side effects to FDA at 1-800-FDA-1088.

How should I store EMEND?

- Store EMEND at room temperature, between 68°F and 77°F (20°C and 25°C).
- Keep EMEND and all medicines out of the reach of children.

General information about EMEND

Medicines are sometimes prescribed for conditions that are not mentioned in patient information leaflets. Do not use EMEND for a condition for which it was not prescribed. Do not give EMEND to other people, even if they have the same symptoms you have. It may harm them.

This Patient Information leaflet summarizes the most important information about EMEND. If you would like to know more information, talk with your doctor. You can ask your doctor or pharmacist for information about EMEND that is written for health professionals. For more information about EMEND call 1-800-622-4477 or go to www.emend.com.

What are the ingredients in EMEND?

Active ingredient: aprepitant

Inactive ingredients: sucrose, microcrystalline cellulose, hydroxypropyl cellulose and sodium lauryl sulfate. The capsule shell excipients are gelatin, titanium dioxide, and may contain sodium lauryl sulfate and silicon dioxide. The 125-mg capsule shell also contains red ferric oxide and yellow ferric oxide. The 40-mg capsule shell also contains yellow ferric oxide.

U.S. Patent Nos.: 5,145,684; 5,719,147; 6,048,859; 6,096,742; 6,235,735

The brands listed in the above sections “Who should not take EMEND?” and “What should I tell my doctor before and during treatment with EMEND?” are the registered trademarks of their respective owners and are not trademarks of Merck Sharp & Dohme Corp., a subsidiary of Merck & Co., Inc.

EMEND® is a registered trademark of Merck Sharp & Dohme Corp., a subsidiary of Merck & Co., Inc.
Copyright © 2003, 2005, 2006 Merck Sharp & Dohme Corp., a subsidiary of Merck & Co., Inc.
All rights reserved

Issued March 2011

Merck Sharp & Dohme Corp., a subsidiary of Merck & Co., Inc.
Whitehouse Station, NJ 08889, USA

9988902

Repackaged by:

Rebel Distributors Corp
Thousand Oaks, CA 91320